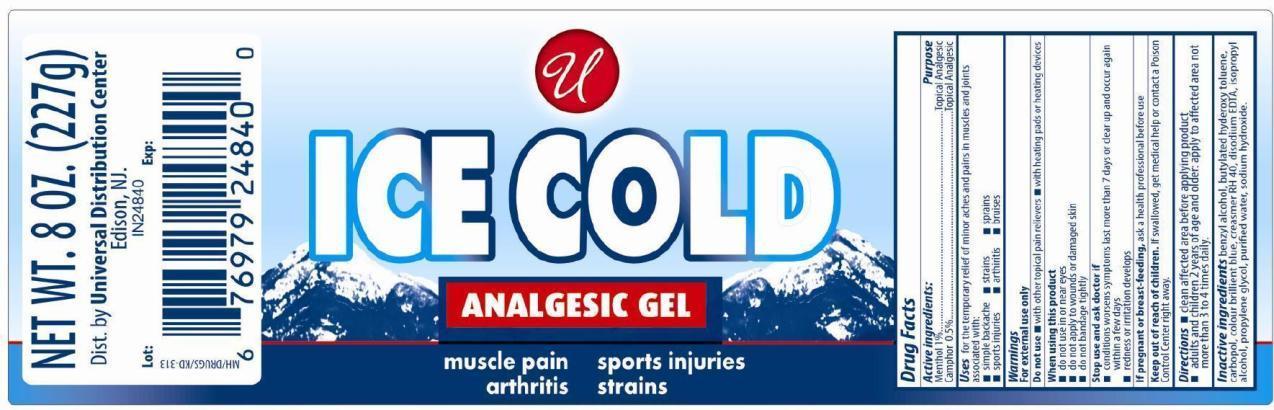 DRUG LABEL: Ice Cold Analgesic Gel
NDC: 52000-013 | Form: GEL
Manufacturer: Universal Distribution Center LLC
Category: otc | Type: HUMAN OTC DRUG LABEL
Date: 20241204

ACTIVE INGREDIENTS: MENTHOL, UNSPECIFIED FORM 1 g/100 g; CAMPHOR (SYNTHETIC) 0.5 g/100 g
INACTIVE INGREDIENTS: BENZYL ALCOHOL; BUTYLATED HYDROXYTOLUENE; CARBOMER HOMOPOLYMER TYPE B (ALLYL SUCROSE CROSSLINKED); FD&C BLUE NO. 1; EDETATE DISODIUM; ISOPROPYL ALCOHOL; PROPYLENE GLYCOL; SODIUM HYDROXIDE; WATER

Ice Cold Anagelsic Gel

Active Ingredients

Menthol 1.0%

Camphor 0.5%

Purpose

Topical Analgesic

Uses

for the temporary relief of minor aches and pains in muscles and joints associated with:

- simple backache
- strains
- sprains
- sports injuries
- arthritis
- bruises

Warnings

For external use only

Do not use

- with other topical pain relievers
- with heating pads or heating devices

When using this product

- do not use in or near eyes
- do not apply to wounds or damaged skin
- do not bandage tightly

Stop use and ask doctor if

- condition worsens
- symptoms last more than 7 days or clean up and occur again within a few days
- redness or irritation develops

PREGNANCY OR BREAST FEEDING

If pregnant or breast-feeding, ask a health professional before use

Keep out of the reach of children

If swallowed, get medical help or contact a Poison Control Center right away

Directions

- clean affected area before applying product
- adults and children 2 years of age and older: apply to affected area not more than 3 to 4 times daily

Inactive ingredients

benzyl alcohol, butylated hydroxytoluene, carbopol, colour brillient blue, creasmer RH 40, disodium EDTA, isopropyl alcohol, propylene glycol, purified water and sodium hydroxide

PRINCIPAL DISPLAY PANEL

ICE COLD ANALGESIC GEL

Topical Analgesic
NET WT.8 OZ (227g)